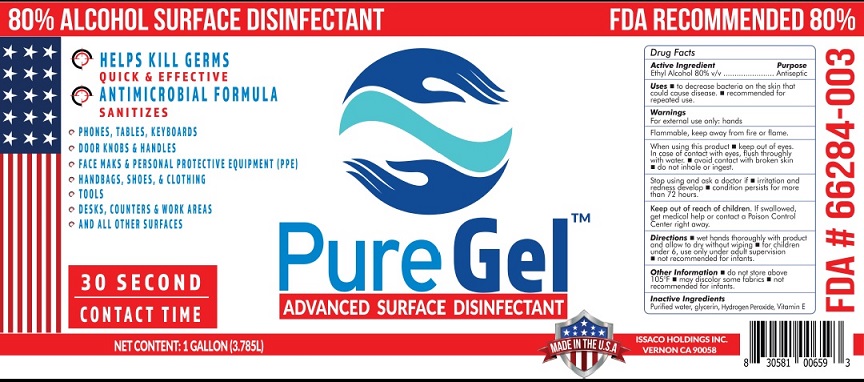 DRUG LABEL: PureGel Advanced Surface Disinfectant
NDC: 75494-004 | Form: LIQUID
Manufacturer: Alchemy Nutra LLC
Category: otc | Type: HUMAN OTC DRUG LABEL
Date: 20200519

ACTIVE INGREDIENTS: ALCOHOL 80 mL/100 mL
INACTIVE INGREDIENTS: GLYCERIN; .ALPHA.-TOCOPHEROL; WATER; HYDROGEN PEROXIDE

Active Ingredient

Ethyl Alcohol 80% v/v.

Purpose

Antiseptic

Uses

- To decrease bacteria on the skin that could cause disease.
- recommended for repeated use

Warnings

For external use only: hands

Flammable, keep away from fire or flame

When using this product • keep out of eyes. In case of contact with eyes, flush throughlywith water.

•Avoid contact with broken skin.

• Do not inhale or ingest.

Stop using and ask a doctor if • irritation and redness develops • condition persists for more than 72 hours.

Keep out of reach of children

If swallowed, get medical help or contact a Poison Control Center right away.

Directions

• Wet hands thoroughly with product and allow to dry without wiping • For children under 6, use only under adult supervision •Not recommended for infants

Other Information: • Do not store above 105°F. •may discolor some fabrics.

Inactive ingredients

Purified water, glycerin, Hydrogen Peroxide, Vitamin E